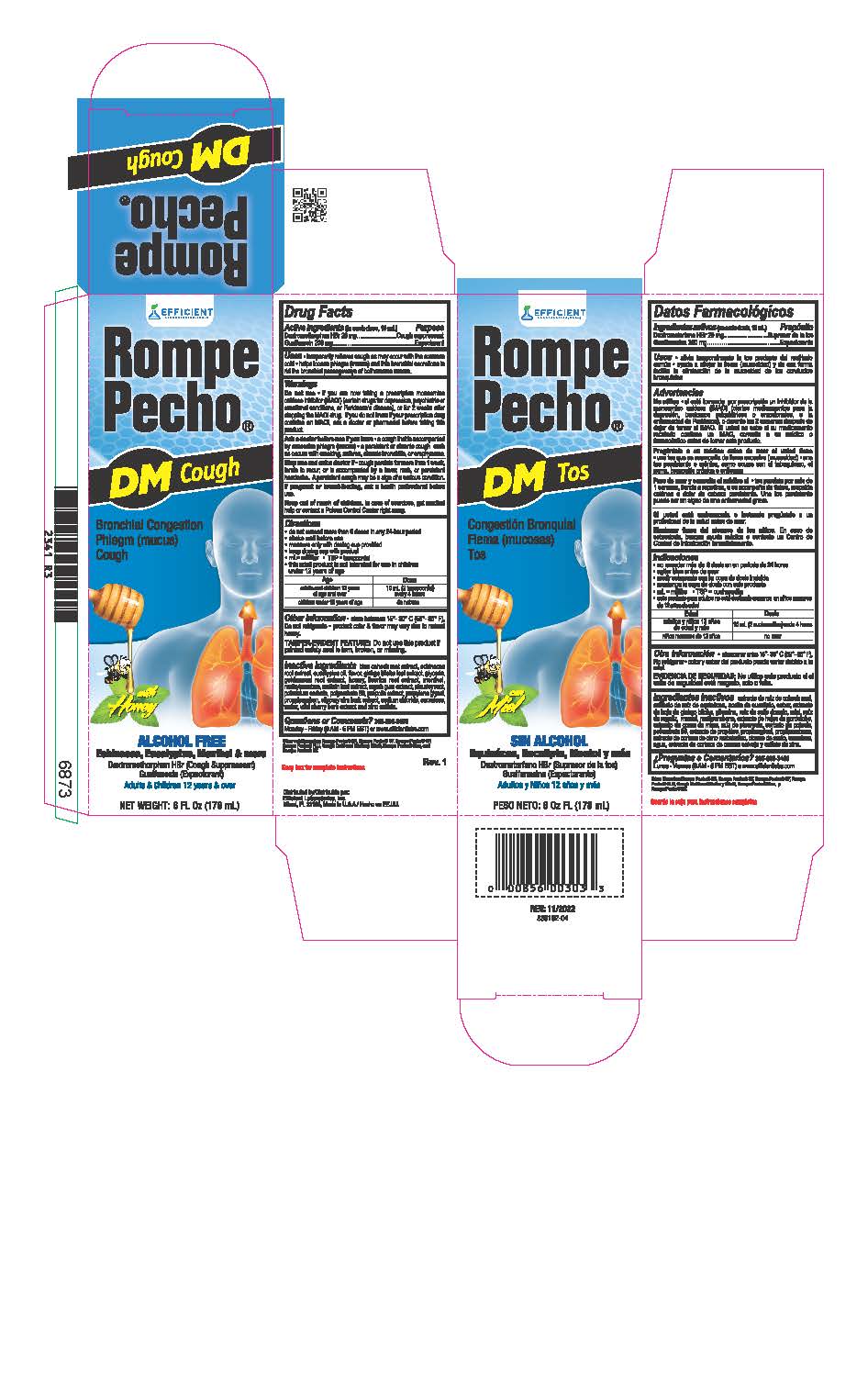 DRUG LABEL: Rompe Pecho
NDC: 58593-275 | Form: LIQUID
Manufacturer: Efficient Laboratories Inc
Category: otc | Type: HUMAN OTC DRUG LABEL
Date: 20251014

ACTIVE INGREDIENTS: DEXTROMETHORPHAN HYDROBROMIDE 10 mg/5 mL; GUAIFENESIN 100 mg/5 mL
INACTIVE INGREDIENTS: SUCRALOSE; PROPOLIS WAX; CAULOPHYLLUM THALICTROIDES ROOT; ECHINACEA, UNSPECIFIED; EUCALYPTUS GLOBULUS LEAF; GINKGO; GOLDENSEAL; HONEY; GLYCYRRHIZA GLABRA; MENTHOL; METHYLPARABEN; VERBASCUM DENSIFLORUM LEAF; MYRRH; ASCLEPIAS TUBEROSA ROOT; POTASSIUM SORBATE; PROPYLENE GLYCOL; PROPYLPARABEN; WATER; ULMUS RUBRA BARK; SODIUM CHLORIDE; SPEARMINT; PRUNUS SEROTINA BARK; ZINC SULFATE; GLYCERIN

Rompe Pecho

Active Ingredients:(in each teaspoonful 5 ml.) Purpose

Dextromethorphan Hydrobromide 10 mg ...................................... Cough Suppressant

Guaifenesin 100 mg ................................................................... Expectorant

Purpose

Cough Suppressant

Expectorant

Uses:

- temporarily relieves cough as may occur with the common cold
- helps loosen phlegm (mucus) and thin bronchial secretions to rid the bronchial passageways of bothersome mucus.

Warnings

Do not exceed recommended dosage.

Ask a doctor before use if you have

- a cough that is accompanied by excessive phlegm (mucus)
- a persistent or chronic cough such as occurs with smoking, asthma, chronic bronchitis, or emphysema.

Do not use

- if you are now taking a prescription monoamine oxidase inhibitor (MAOI) (certain drugs for depression, psychiatric, or emotional conditions, or Parkinson's disease), or for 2 weeks after stopping the MAOI drug. If you do not know if your prescription drug contains on MAOI, ask a doctor or pharmacist before taking this product.

- Stop use and ask a doctor
- If cough persists more than 1 week, tends to recur or is accompanied by a fever, rash or persistent headache. A persistent cough may be a sign of a serious condition.

PREGNANCY OR BREAST FEEDING

If pregnant or breast-feeding,ask a health professional before use.

Keep out of reach of children.

In case of accidental overdose, get medical help or contact a Poison Control Center right away.

Directions

Shake well before use

Do not exceed more than 6 doses in any 24 hour period or as directed by a doctor

Age Dose

Adults and Children 12 years of age and over 10 mL (2 tsps.) every 4 hours

Children 6 to under 12 years of age 5 mL (1 tsp.) every 4 hours

Children under 6 years of age Do not use

INACTIVE INGREDIENT

Inactive Ingredients: Blue Cohosh root extract, Echinacea root extract, Eucalyptus oil, Gingka Biloba leaf extract, glycerin, Golden Seal Root extract, Honey, Licorice Root extract, Menthol, Methylparaben, Mullein leaf extract, Myrrh gum extract, Pleurisy Root, Potassium sorbate, polysorbate 80, propolis extract, propylene glycol, Propylparaben, Slippery Elm Bark extract, Sodium Chloride, Spearmint flavor, Sucralose, water, Wild Cherry Bark extract and Zinc Sulfate.

Questions or Comments?

305-805-3456 Monday - Friday 9AM to 5PM EST

www.efficientlabs.com